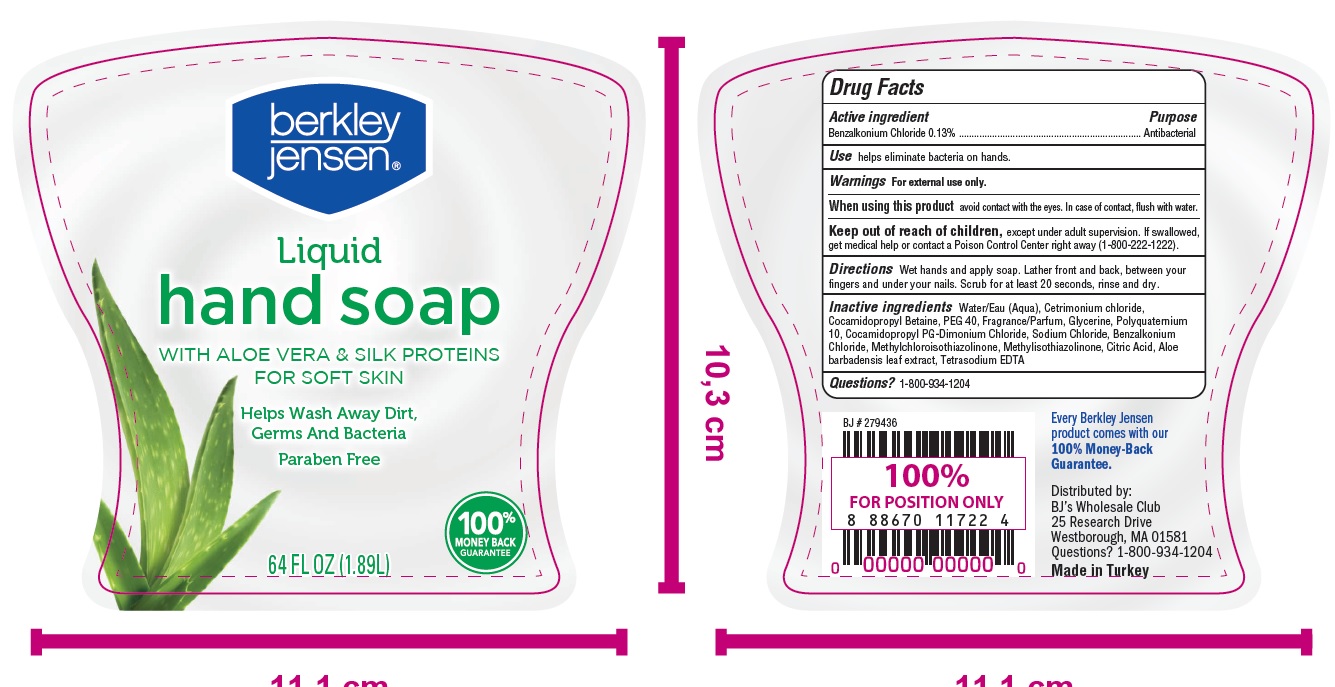 DRUG LABEL: Antibacterial
NDC: 76772-030 | Form: LIQUID
Manufacturer: TSM ITHALAT IHRACAT SANAYI VE DIS TICARET LIMITED SIRKETI
Category: otc | Type: HUMAN OTC DRUG LABEL
Date: 20210719

ACTIVE INGREDIENTS: BENZALKONIUM CHLORIDE 1.3 g/1 mL
INACTIVE INGREDIENTS: WATER; CETRIMONIUM CHLORIDE; SODIUM LAURETH SULFATE; COCAMIDOPROPYL BETAINE; POLYQUATERNIUM-10 (1000 MPA.S AT 2%); SODIUM CHLORIDE; METHYLISOTHIAZOLINONE; GLYCERIN; COCAMIDOPROPYL PG-DIMONIUM CHLORIDE; METHYLCHLOROISOTHIAZOLINONE; CITRIC ACID ACETATE; ALOE VERA LEAF; EDETATE SODIUM

Berkley Jensen Liquid Hand Soap -Aloe vera & Silk proteins For Soft Skin

Active ingredients

Benzalkonium chloride 0.13%.................Anitbacterial Hand soap

Purpose

Antibacterial Hand Soap

Use

help eliminate bacteria on hands.

Warnings

For external use only: hands only

When using this product

- avoid contact with eyes. If contact occurs, rinse eyes with water

Stop use and ask a doctor if

- irritation or redness develops
- condition persists for more than 72 hours

Keep out of reach of children

- Except under adult supervision.
- If swallowed, get medical help or contact a Poison Control Center right away

Directions

- Wet hand and apply soap.
- Lather front and back between your fingers and under your nails.
- Scrub for at least 20 second
- rinse and dry.

INACTIVE INGREDIENT

Water, Cetrimonium chloride , Cocamidopropyl betaine, Sodium chloride, glycerin,PEG-40

Fragrance, Polyquatemium-10 , PEG-8 , Citric Acid, Tetrasodium EDTA, Cocamidopropyl PG-Dimonium Chrolide,

Methylchloroisothiazolinone, Methlisothiazolinone, Aloe Vera